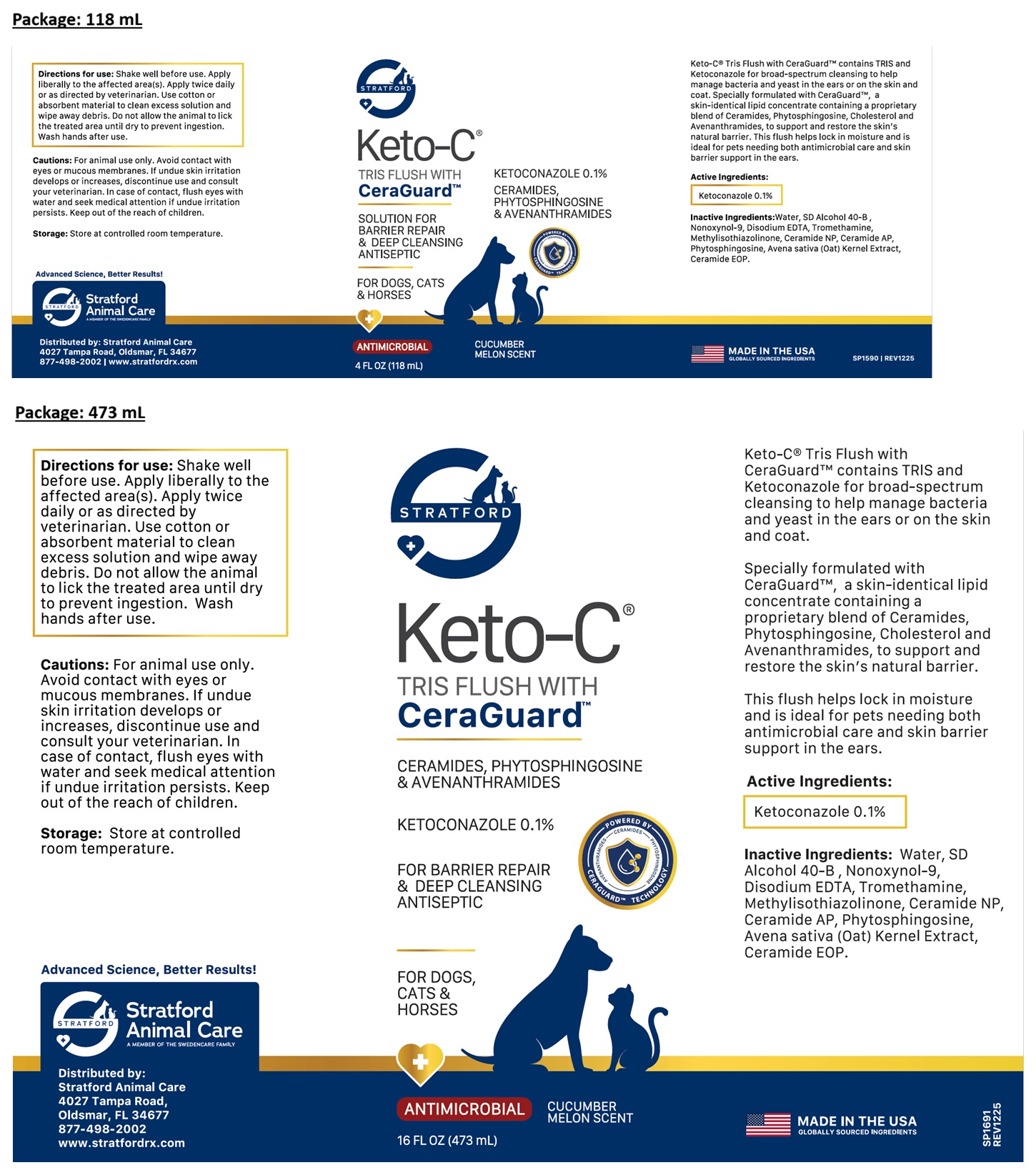 DRUG LABEL: STRATFORD Keto-C TRIS FLUSH WITH CeraGuard
NDC: 86069-141 | Form: SOLUTION
Manufacturer: Stratford Care Usa, Inc.
Category: animal | Type: OTC ANIMAL DRUG LABEL
Date: 20260204

ACTIVE INGREDIENTS: KETOCONAZOLE 0.1 g/100 mL
INACTIVE INGREDIENTS: WATER; ALCOHOL; NONOXYNOL-9; EDETATE DISODIUM; TROMETHAMINE; METHYLISOTHIAZOLINONE; CERAMIDE NP; CERAMIDE AP; PHYTOSPHINGOSINE; OAT; CERAMIDE 9

STRATFORD Keto-C® TRIS FLUSH WITH CeraGuard™

Keto-C® Tris Flush with CeraGuard™ contains TRIS and Ketoconazole for broad-spectrum cleansing to help manage bacteria and yeast in the ears or on the skin and coat.

Specially formulated with CeraGuard™, a skin-identical lipid concentrate containing a proprietary blend of Ceramides, Phytosphingosine, Cholesterol and Avenanthramides, to support and restore the skin's natural barrier.

This flush helps lock in moisture and is ideal for pets needing both antimicrobial care and skin barrier support in the ears.

Active Ingredients:

Ketoconazole 0.1%

Inactive Ingredients:

Water, SD Alcohol 40-B, Nonoxynol-9, Disodium EDTA, Tromethamine, Methylisothiazolinone, Ceramide NP, Ceramide AP, Phytosphingosine, Avena sativa (Oat) Kernel Extract, Ceramide EOP.

Directions for use:

Shake well before use. Apply liberally to the affected area(s). Apply twice daily or as directed by veterinarian. Use cotton or absorbent material to clean excess solution and wipe away debris. Do not allow the animal to lick the treated area until dry to prevent ingestion. Wash hands after use.

Cautions:

For animal use only. Avoid contact with eyes or mucous membranes. If undue skin irritation develops or increases, discontinue use and consult your veterinarian. In case of contact, flush eyes with water and seek medical attention if undue irritation persists. Keep out of the reach of children.

Storage:

Store at controlled room temperature.

CERAMIDES, PHYTOSPHINGOSINE & AVENANTHRAMIDES

SOLUTION FOR BARRIER REPAIR & DEEP CLEANSING ANTISEPTIC

FOR DOGS, CATS & HORSES

ANTIMICROBIAL

CUCUMBER MELON SCENT

MADE IN THE USA
GLOBALLY SOURCED INGREDIENTS

Advanced Science, Better Results!

Stratfordare Animal Care
A MEMBER OF THE SWEDENCARE FAMILY

Distributed by:
Stratford Animal Care
4027 Tampa Road,
Oldsmar, FL 34677
877-498-2002
www.stratfordrx.com